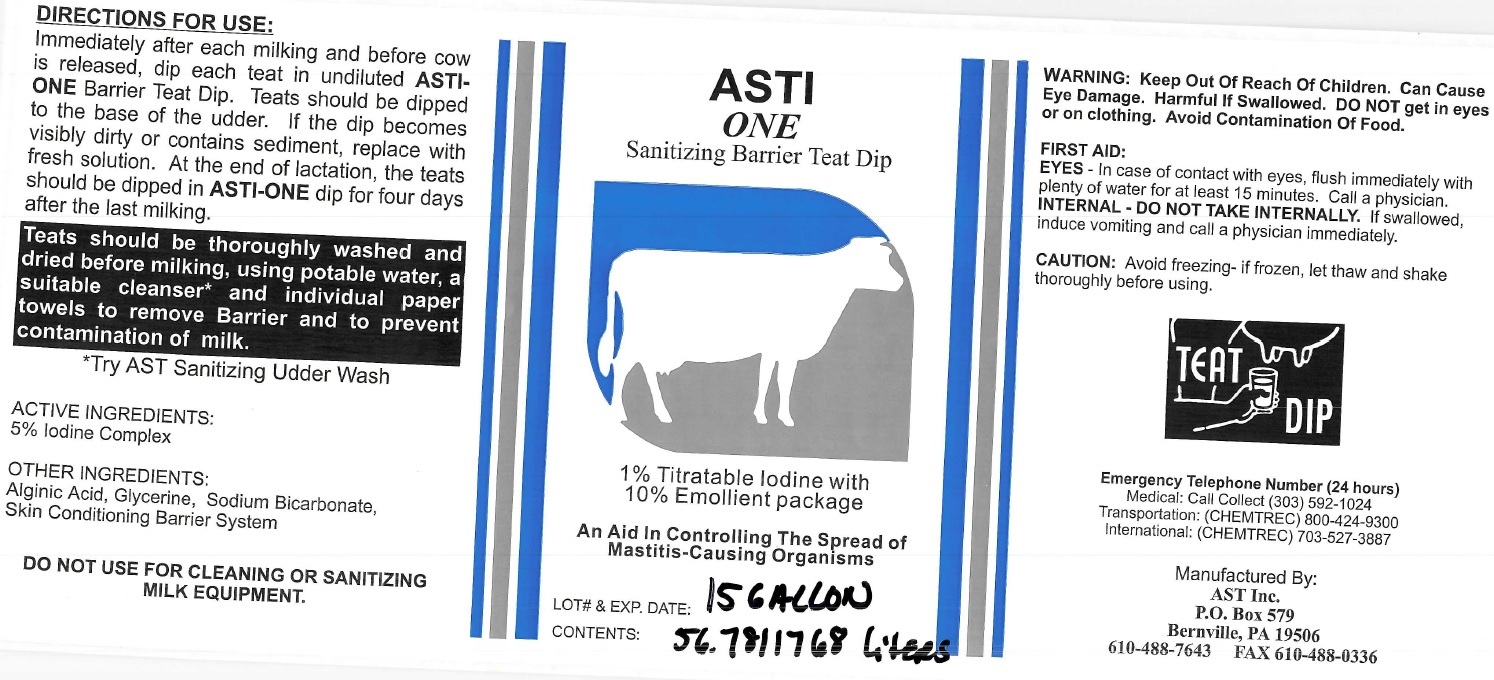 DRUG LABEL: ASTI ONE Sanitizing Barrier Teat Dip
NDC: 52657-0105 | Form: SOLUTION
Manufacturer: Advanced Skin Technologies Inc.
Category: animal | Type: OTC ANIMAL DRUG LABEL
Date: 20220219

ACTIVE INGREDIENTS: IODINE 50 mg/0.001 L
INACTIVE INGREDIENTS: ALGINIC ACID; GLYCERIN; SODIUM BICARBONATE

ASTI ONE Sanitizing Barrier Teat Dip

WARNING:

Can Cause Eye Damage. Harmful If swallowed. DO NOT get in eyes or on clothing. Avoid Contamination Of Food.

FIRST AID:

EYES - In case of contact with eyes, flush immediately with plenty of water for at least 15 minutes. Call a physician..

INTERNAL -DO NOT TAKE INTERNALLY. If swallowed, induce vomiting and call a physician immediately.

CAUTION:

Avoid freezing - If frozen, let thaw and shake thoroughly before using.

DIRECTIONS FOR USE:

Immediately after each milking and before cow is released, dip each teat in undiluted ASTI-ONE Barrier Teat Dip. Teats should be dipped to the base of the udder. If the dip becomes visibly dirty or contains sediment, replace with fresh solution. At the end of lactation, the teats should be dipped in ASTI-ONE dip for four days after the last milking.

(*with AST Udder Wash or similar)

Teats should be thoroughly washed and dried before milking, using potable water, a suitable cleanser* and individual paper towels to remove Barrier and to prevent contamination of milk.

*Try AST Sanitizing Udder Wash

ACTIVE INGREDIENTS:

5% Iodine Complex

OTHER INGREDIENTS:

Alginic Acid, Glycerine, Sodium Bicarbonate, Skin Conditioning Barrier System

DO NOT USE FOR CLEANING OR SANITIZING MILK EQUIPMENT.